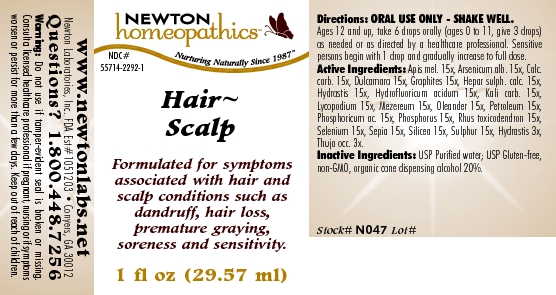 DRUG LABEL: Hair Scalp 
NDC: 55714-2292 | Form: LIQUID
Manufacturer: Newton Laboratories, Inc.
Category: homeopathic | Type: HUMAN OTC DRUG LABEL
Date: 20110301

ACTIVE INGREDIENTS: Apis Mellifera 15 [hp_X]/1 mL; Arsenic Trioxide 15 [hp_X]/1 mL; Oyster Shell Calcium Carbonate, Crude 15 [hp_X]/1 mL; Solanum Dulcamara Top 15 [hp_X]/1 mL; Graphite 15 [hp_X]/1 mL; Calcium Sulfide 15 [hp_X]/1 mL; Goldenseal 15 [hp_X]/1 mL; Hydrofluoric Acid 15 [hp_X]/1 mL; Potassium Carbonate 15 [hp_X]/1 mL; Lycopodium Clavatum Spore 15 [hp_X]/1 mL; Daphne Mezereum Bark 15 [hp_X]/1 mL; Nerium Oleander Leaf 15 [hp_X]/1 mL; Kerosene 15 [hp_X]/1 mL; Phosphoric Acid 15 [hp_X]/1 mL; Phosphorus 15 [hp_X]/1 mL; Toxicodendron Pubescens Leaf 15 [hp_X]/1 mL; Selenium 15 [hp_X]/1 mL; Sepia Officinalis Juice 15 [hp_X]/1 mL; Silicon Dioxide 15 [hp_X]/1 mL; Sulfur 15 [hp_X]/1 mL; Thuja Occidentalis Leafy Twig 3 [hp_X]/1 mL
INACTIVE INGREDIENTS: Alcohol

Hair - Scalp

INDICATIONS & USAGE SECTION

Hair - Scalp Formulated for symptoms associated with hair and scalp conditions such as dandruff, hair loss, premature graying, soreness and sensitivity.

DOSAGE & ADMINISTRATION SECTION

Directions: ORAL USE ONLY - SHAKE WELL. Ages 12 and up, take 6 drops orally (ages 0 to 11, give 3 drops) as needed or as directed by a healthcare professional. Sensitive persons begin with 1 drop and gradually increase to full dose.

OTC - ACTIVE INGREDIENT SECTION

Apis mel. 15x, Arsenicum alb. 15x, Calc.carb. 15x, Dulcamara 15x, Graphites 15x, Hepar sulph. calc. 15x, Hydrastis 15x, Hydrofluoricum acidum 15x, Kali carb. 15x, Lycopodium 15x, Mezereum 15x, Oleander 15x, Petroleum 15x, Phosphoricum ac. 15x, Phosphorus 15x, Rhus toxicodendron 15x, Selenium 15x, Sepia 15x, Silicea 15x, Sulphur 15x, Hydrastis 3x,Thuja occ. 3x.

OTC - PURPOSE SECTION

Formulated for symptoms associated with hair and scalp conditions such as dandruff, hair loss, premature graying, soreness and sensitivity.

INACTIVE INGREDIENT SECTION

Inactive Ingredients: USP Purified Water; USP Gluten-free, non-GMO, organic cane dispensing alcohol 20%.

QUESTIONS SECTION

www.newtonlabs.net Newton Laboratories, Inc. FDA Est # 1051203 - Conyers, GA 30012
Questions? 1.800.448.7256

WARNINGS SECTION

Warning: Do not use if tamper - evident seal is broken or missing. Consult a licensed healthcare professional if pregnant, nursing or if symptoms worsen or persist for more than a few days. Keep out of reach of children.

OTC - PREGNANCY OR BREAST FEEDING SECTION

Consult a licensed healthcare professional if pregnant, nursing or if symptoms worsen or persist for more than a few days.

OTC - KEEP OUT OF REACH OF CHILDREN SECTION

Keep out of reach of children.